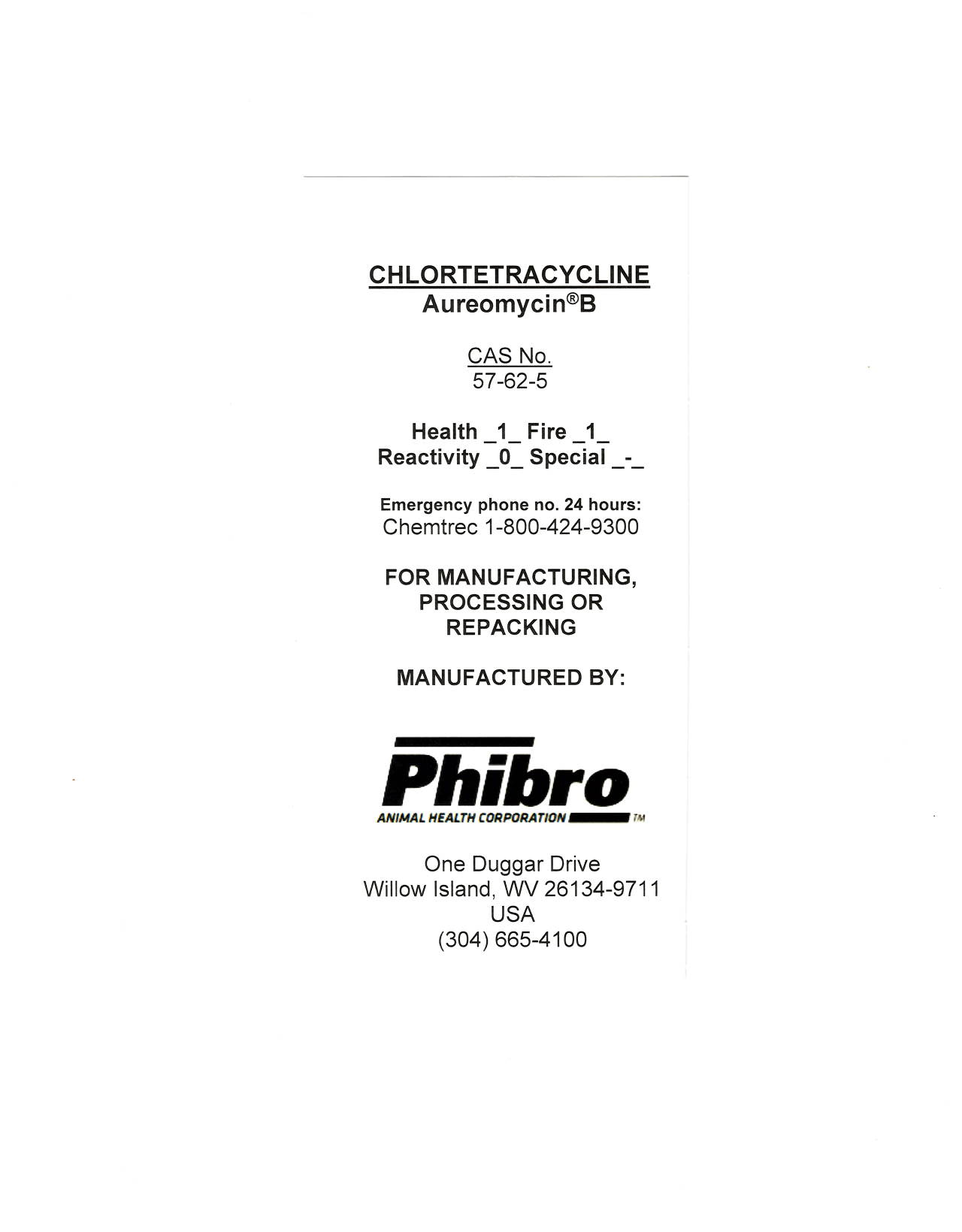 DRUG LABEL: Chlortetracycline
NDC: 66104-4396 | Form: POWDER
Manufacturer: Phibro Animal Health
Category: other | Type: BULK INGREDIENT - ANIMAL DRUG
Date: 20260204

ACTIVE INGREDIENTS: CHLORTETRACYCLINE 50 kg/50 kg

Chlortetracycline

CHLORTETRACYCLINE - Aureomycin®B

CAS No.

57-62-5

Health_1_Fire_1_

Reactivity_0_Special_-_

Emergency phone no. 24 hours:

Chemtrec 1-800-424-9300

FOR MANUFACTURING, PROCESSING OR REPACKING

MANUFACTURED BY:

PHIBRO ANIMAL HEALTH CORPORATION

One Duggar Drive

Willow Island, WV 36134-9711

USA

304-665-4100

Chlortetracycline Label

Label